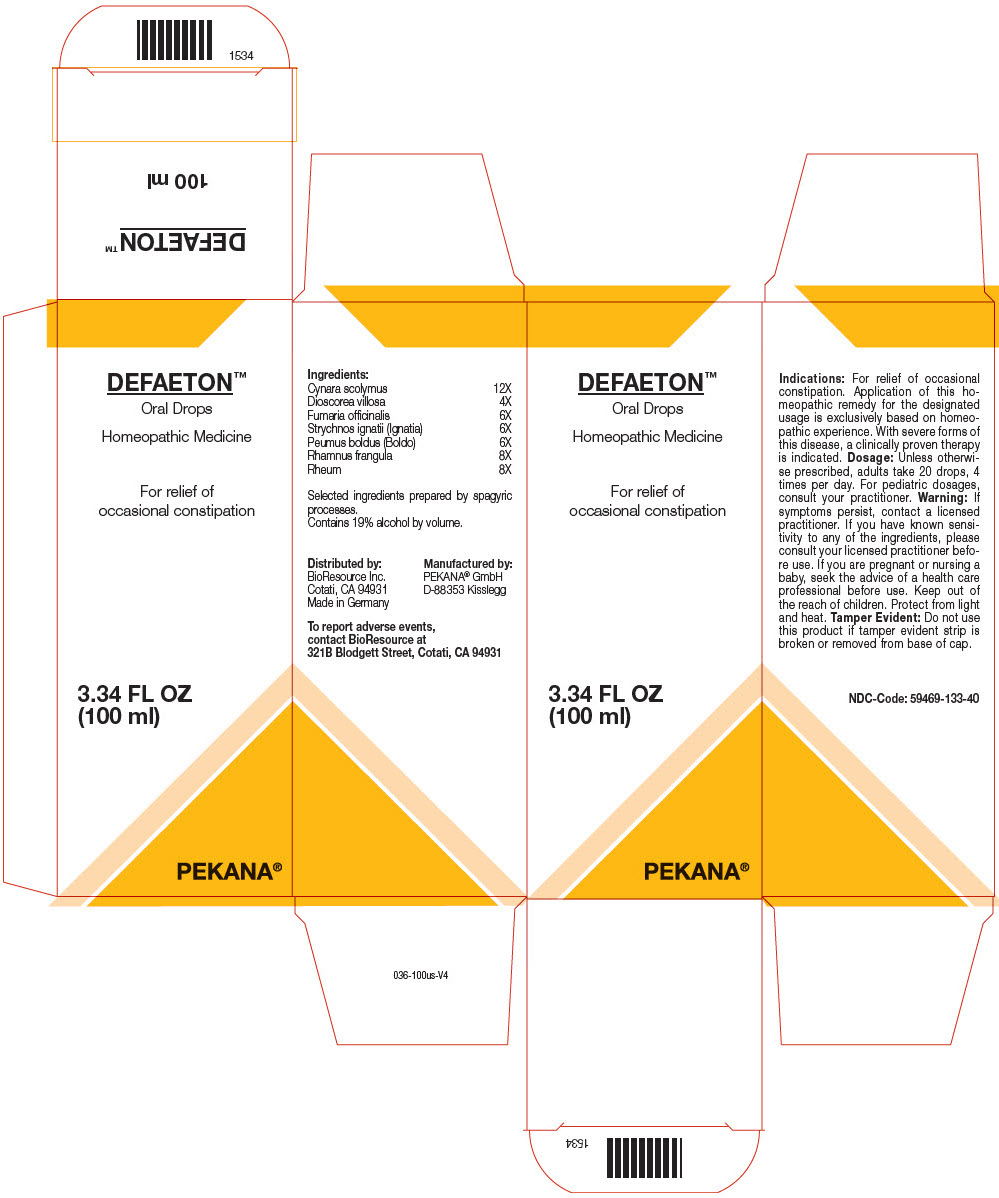 DRUG LABEL: DEFAETON
NDC: 59469-133 | Form: SOLUTION/ DROPS
Manufacturer: PEKANA Naturheilmittel GmbH
Category: homeopathic | Type: HUMAN OTC DRUG LABEL
Date: 20230111

ACTIVE INGREDIENTS: PEUMUS BOLDUS LEAF 6 [hp_X]/50 mL; DIOSCOREA VILLOSA TUBER 4 [hp_X]/50 mL; STRYCHNOS IGNATII SEED 6 [hp_X]/50 mL; CYNARA SCOLYMUS WHOLE 12 [hp_X]/50 mL; FUMARIA OFFICINALIS WHOLE 6 [hp_X]/50 mL; FRANGULA ALNUS BARK 8 [hp_X]/50 mL; RHEUM OFFICINALE ROOT 8 [hp_X]/50 mL
INACTIVE INGREDIENTS: WATER; ALCOHOL

DEFAETON™

ACTIVE INGREDIENT

Ingredients:
Cynara scloymus | 12X
Dioscorea villosa | 4X
Fumaria officinalis | 6X
Strychnos ignatii (Ignatia) | 6X
Peumus boldus (Boldo) | 6X
Rhamnus frangula | 8X
Rheum | 8X

Selected ingredients prepared by spagyric processes.

INACTIVE INGREDIENT

Contains 19% alcohol by volume.

Indications

PURPOSE

For relief of occasional constipation. Application of this homeopathic remedy for the designated usage is exclusively based on homeopathic experience. With severe forms of this disease, a clinically proven therapy is indicated.

Dosage

Unless otherwise prescribed, adults take 20 drops, 4 times per day. For pediatric dosages, consult your practitioner.

Warning

If symptoms persist, contact a licensed practitioner. If you have known sensitivity to any of the ingredients, please consult your licensed practitioner before use. If you are pregnant or nursing a baby, seek the advice of a health care professional before use.

Keep out of the reach of children.

STORAGE AND HANDLING

Protect from light and heat.

Tamper Evident

Do not use this product if tamper evident strip is broken or removed from base of cap.

QUESTIONS

To report adverse events, contact BioResource at 321B Blodgett Street, Cotati, CA 94931

Distributed by:
BioResource Inc.
Cotati, CA 94931

Manufactured by:
PEKANA® GmbH
D-88353 Kisslegg

PRINCIPAL DISPLAY PANEL - 100 ml Bottle Box

DEFAETON™
Oral Drops

Homeopathic Medicine

For relief of
occasional constipation

3.34 FL OZ
(100 ml)

PEKANA®